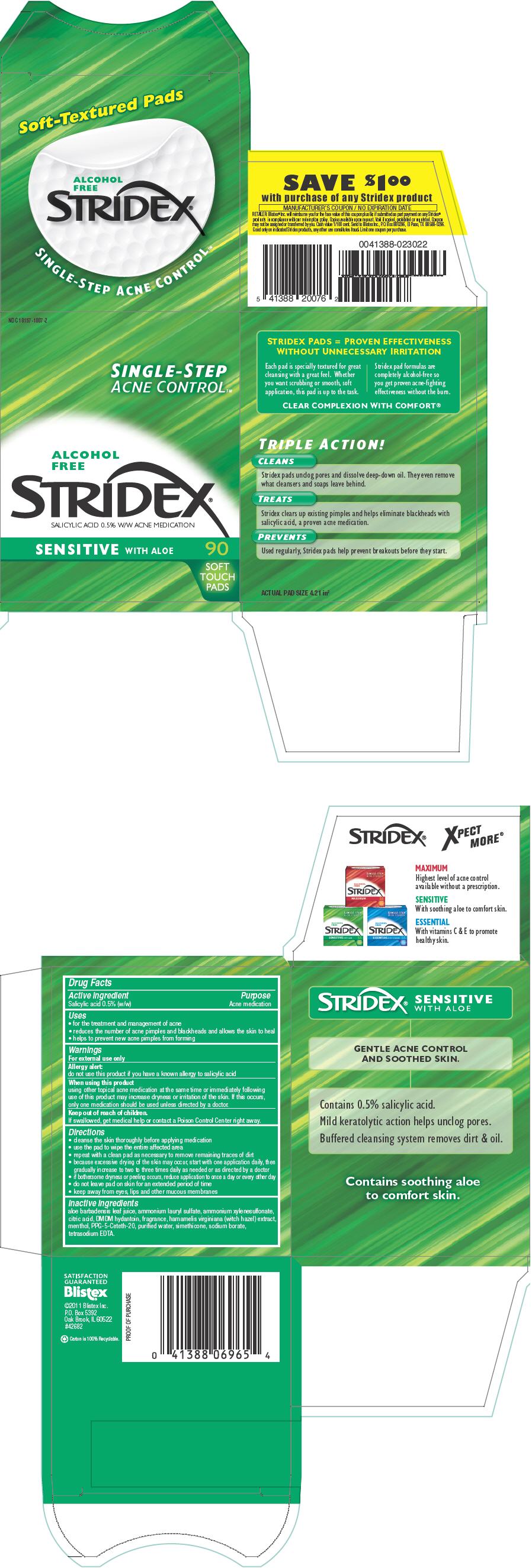 DRUG LABEL: Stridex 
NDC: 10157-1007 | Form: LIQUID
Manufacturer: Blistex Inc
Category: otc | Type: HUMAN OTC DRUG LABEL
Date: 20241212

ACTIVE INGREDIENTS: Salicylic Acid 0.5 g/100 mL
INACTIVE INGREDIENTS: aloe vera leaf; ammonium lauryl sulfate; ammonium xylenesulfonate; citric acid monohydrate; DMDM hydantoin; hamamelis virginiana top; MENTHOL, UNSPECIFIED FORM; PPG-5-ceteth-20; water; sodium borate; edetate sodium

Stridex®
Sensitive

Drug Facts

Active ingredient

Salicylic acid 0.5% (w/w)

Purpose

Acne medication

Uses

- for the treatment and management of acne
- reduces the number of acne pimples and blackheads and allows the skin to heal
- helps to prevent new acne pimples from forming

Warnings

For external use only

Allergy alert

do not use this product if you have a known allergy to salicylic acid

When using this product

using other topical acne medication at the same time or immediately following use of this product may increase dryness or irritation of the skin. If this occurs, only one medication should be used unless directed by a doctor.

Keep out of reach of children.

If swallowed, get medical help or contact a Poison Control Center right away.

Directions

- cleanse the skin thoroughly before applying medication
- use the pad to wipe the entire affected area
- repeat with a clean pad as necessary to remove remaining traces of dirt
- because excessive drying of the skin may occur, start with one application daily, then gradually increase to two to three times daily as needed or as directed by a doctor
- if bothersome dryness or peeling occurs, reduce application to once a day or every other day
- do not leave pad on skin for an extended period of time
- keep away from eyes, lips and other mucous membranes

Inactive ingredients

aloe barbadensis leaf juice, ammonium lauryl sulfate, ammonium xylenesulfonate, citric acid, DMDM hydantoin, fragrance, hamamelis virginiana (witch hazel) extract, menthol, PPG-5-Ceteth-20, purified water, simethicone, sodium borate, tetrasodium EDTA.

PRINCIPAL DISPLAY PANEL - 90 Pad Jar Carton

NDC 10157-1007-2

SINGLE-STEP
ACNE CONTROL™

ALCOHOL
FREE

STRIDEX®
SALICYLIC ACID 0.5% W/W ACNE MEDICATION

SENSITIVE WITH ALOE

90

SOFT
TOUCH
PADS